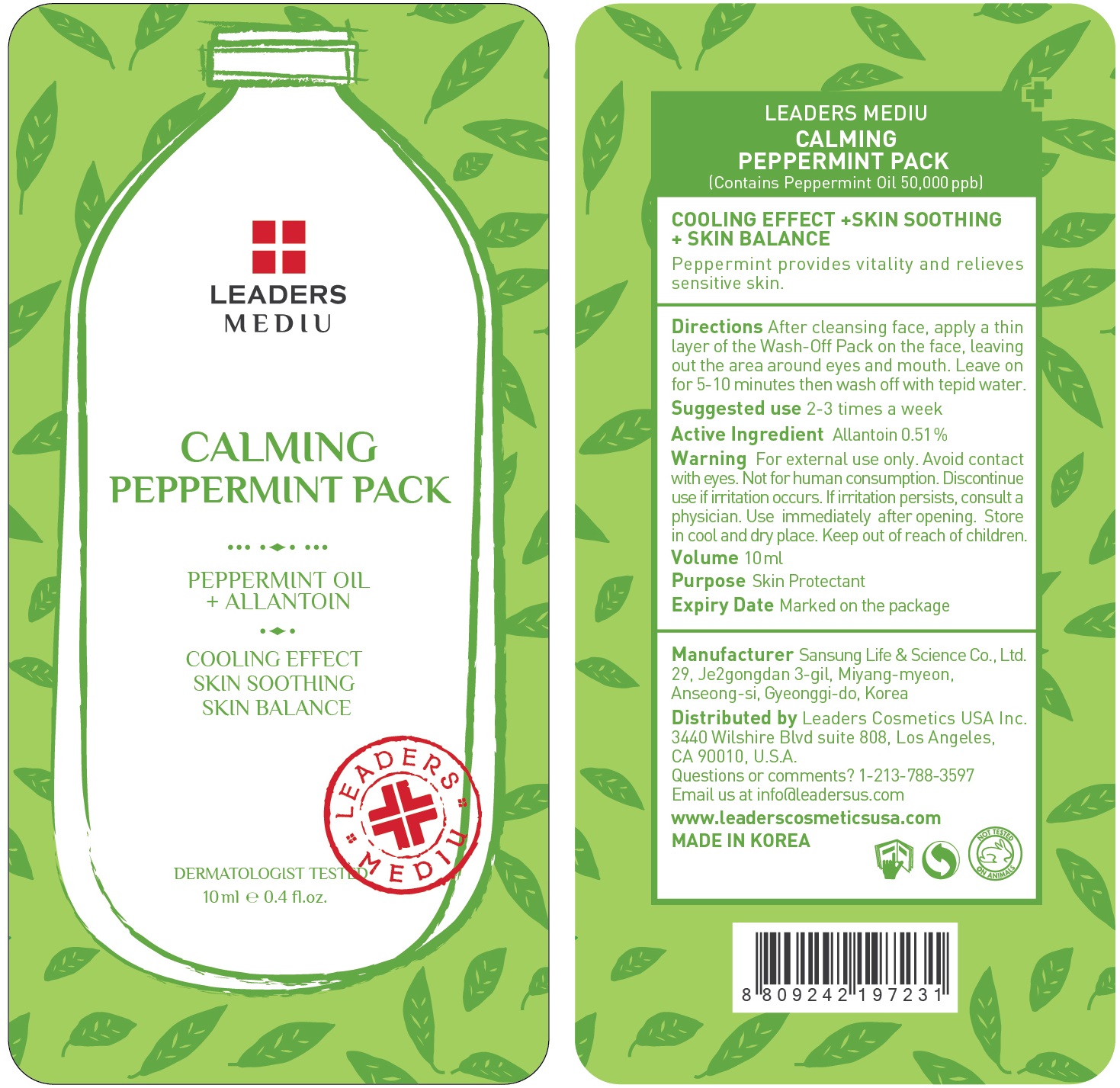 DRUG LABEL: LEADERS MEDIU CALMING PEPPERMINT PACK
NDC: 69424-450 | Form: GEL
Manufacturer: SANSUNG LIFE & SCIENCE CO., LTD.
Category: otc | Type: HUMAN OTC DRUG LABEL
Date: 20160201

ACTIVE INGREDIENTS: Allantoin 51.0 mg/10 mL
INACTIVE INGREDIENTS: Water; ADZUKI BEAN

ACTIVE INGREDIENT

Active Ingredient: Allantoin 0.51%

INACTIVE INGREDIENT

Inactive Ingredients: Water, Phaseolus angularis seed powder, Butylene Glycol, Kaolin, Bentonite, Magnesium aluminum silicate, PVP, Cellulose, Caramel, Chromium Oxide greens, Betaine, Titanium dioxide, Aloe barbadensis leaf water, Daucus carota sativa (carrot) root extract, Cucurbita pepo (pumpkin) fruit extract, Disodium EDTA, Mentha piperita (peppermint) oil, Polyacrylamide, C13-14 Isoparaffin, Laureth-7, Phenoxyethanol, Chlorphenesin

PURPOSE

Purpose: Skin Protectant

WARNINGS

Warnings: For external use only. Avoid contact with eyes. Not for human consumption. Discontinue use if irritation occurs. If irritation persists, consult a physician.

Use immediately after opening. Store in cool and dry place. Keep out of reach of children.

KEEP OUT OF REACH OF CHILDREN

Directions

Directions: After cleansing face, apply a thin layer of the Wash-Off Pack on the face, leaving out the area around eyes and mouth. Leave on for 5-10 minutes then wash off with tepid water. *Suggested use is 2-3 times a week

Directions

Directions: After cleansing face, apply a thin layer of the Wash-Off Pack on the face, leaving out the area around eyes and mouth. Leave on for 5-10 minutes then wash off with tepid water. *Suggested use is 2-3 times a week